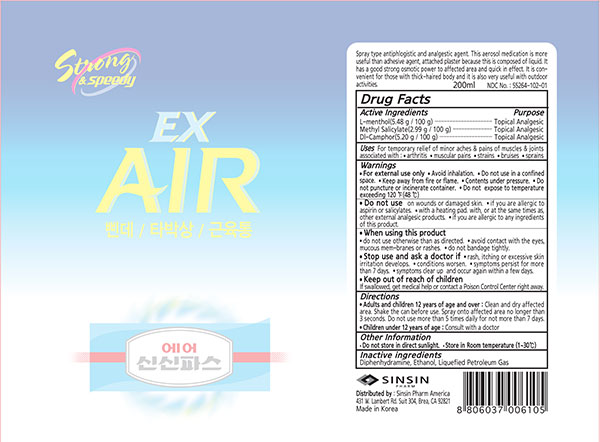 DRUG LABEL: AIR SINSINPAS-EX
NDC: 55264-102 | Form: SPRAY
Manufacturer: Sinsin Pharmaceutical Co., Ltd.
Category: otc | Type: HUMAN OTC DRUG LABEL
Date: 20240105

ACTIVE INGREDIENTS: METHYL SALICYLATE 3.5 g/200 mL; CAMPHOR (SYNTHETIC) 6 g/200 mL; LEVOMENTHOL 6.4 g/200 mL
INACTIVE INGREDIENTS: DIPHENHYDRAMINE; ALCOHOL; LIQUEFIED PETROLEUM GAS

AIR SINSINPAS-EX

Active ingredients

L-menthol (5.48g/100g)

Methyl Salicylate (2.99g/100g)

Dl-Camphor (5.20g/100g)

Purpose

Topical analgesic

Uses

For temporary relief of minor aches & pains of muscles & joints associated with:

- arthritis

- muscular pains

- strains

- bruises

- sprains

Warnings

For external use only • Avoid inhalation. • Do not use in a confined space. • Keep away from fire or flame. • Contents under pressure. • Do not puncture or incinerate container. • Do not expose to temperature exceeding 120 ℉(48 ℃)

Do not use on wounds or damaged skin. • if you are allergic to aspirin or salicylates. • with a heating pad. with, or at the same times as, other external analgesic products. • if you are allergic to any ingredients of this product.

When using this product
• do not use otherwise than as directed. • avoid contact with the eyes, mucous mem-branes or rashes. • do not bandage tightly.

Stop use and ask a doctor if • rash, itching or excessive skin irritation develops. • conditions worsen. • symptoms persist for more than 7 days. • symptoms clear up and occur again within a few days.

Other information

• Do not store in direct sunlight. • Store in Room temperature (1~30℃

Keep out of children

If swallowed, get medical help or contact a Poison Control Center right away.

Directions

• Adults and children 12 years of age and over : Clean and dry affected area. Shake the can before use. Spray onto affected area no longer than 3 seconds. Do not use more than 5 times daily for not more than 7 days.
• Children under 12 years of age : Consult with a doctor

Inactive ingredients

Diphenhydramine, Ethanol, Liquefied Petroleum Gas